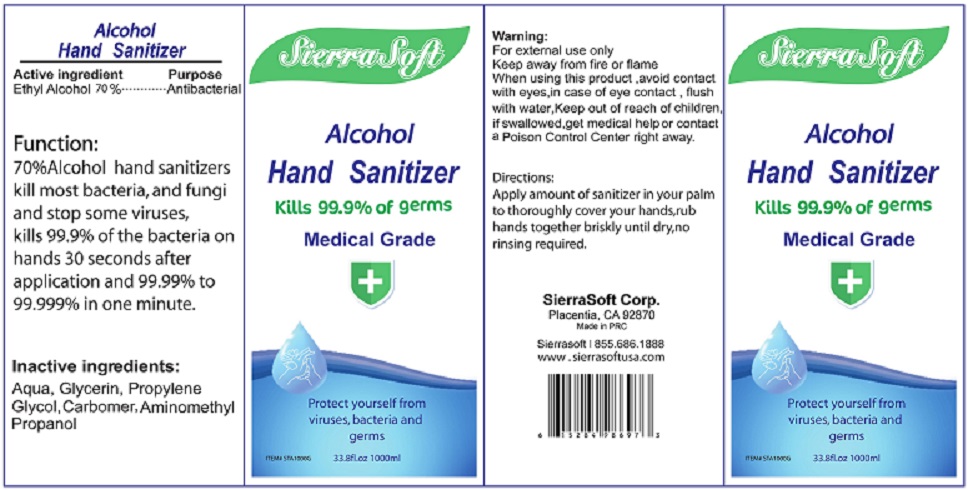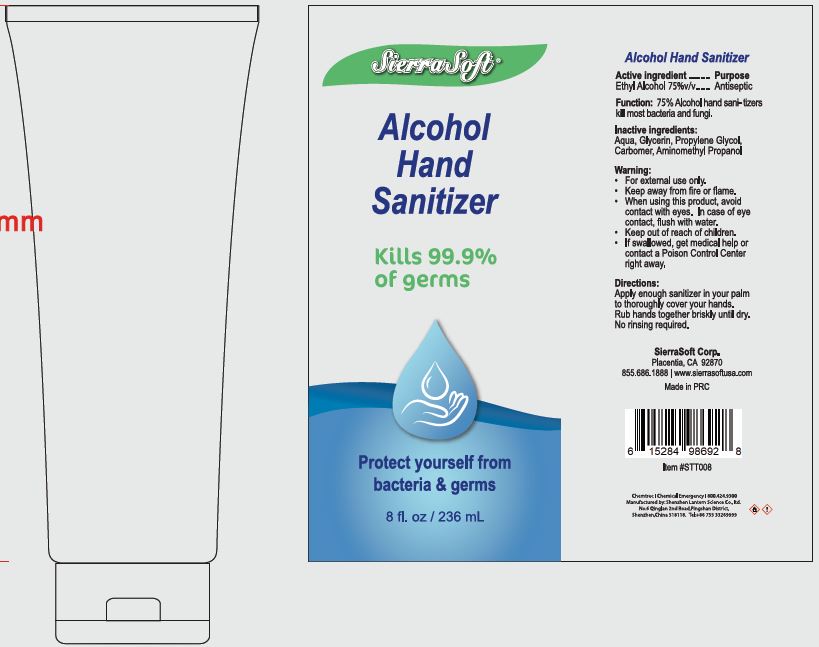 DRUG LABEL: ALCOHOL HAND SANITIZER
NDC: 70415-107 | Form: SOLUTION
Manufacturer: CWGC LA Inc.
Category: otc | Type: HUMAN OTC DRUG LABEL
Date: 20230921

ACTIVE INGREDIENTS: ALCOHOL 70 mL/100 mL
INACTIVE INGREDIENTS: WATER; GLYCERIN; PROPYLENE GLYCOL; CARBOMER HOMOPOLYMER, UNSPECIFIED TYPE; AMINOMETHYLPROPANOL

CWGC (as PLD) - Sierra Soft 70% Alcohol Hand Sanitizer (70415-107)

Active ingredient

Ethyl Alcohol 70 %

PURPOSE

ANTIBACTERIAL

Uses

70% ALCOHOL HAND SANITIZERS KILL MOST BACTERIA, AND FUNGI AND STOP SOME VIRUSES, KILL 99.9% OF THE BACTERIA ON HANDS 30 SECONDS AFTER APPLICATION AND 99.99% TO 99.999% IN ONE MINUTE.

Warnings

FOR EXTERNAL USE ONLY

KEEP AWAY FROM FIRE OR FLAME

WHEN USING THIS PRODUCT, AVOID CONTACT WITH EYES, IN CASE OF EYE CONTACT, FLUSH WITH WATER.

WHEN USING

When using this productavoid contact with eyes. In case of eye contact, flush with water

Keep out of reach of children. If swallowed, get medical help or contact a Poison Control Center right away.

Directions

APPLY AMOUNT OF SANITIZER IN YOUR PALM TO THOROUGHLY COVER YOUR HANDS, RUB HANDS TOGETHER BRISKLY UNTIL DRY, NO RINSING REQUIRED.

Inactive ingredients

AQUA, GLYCERIN, PROPYLENE GLYCOL, CARBOMER, AMINOMETHYL PROPANOL